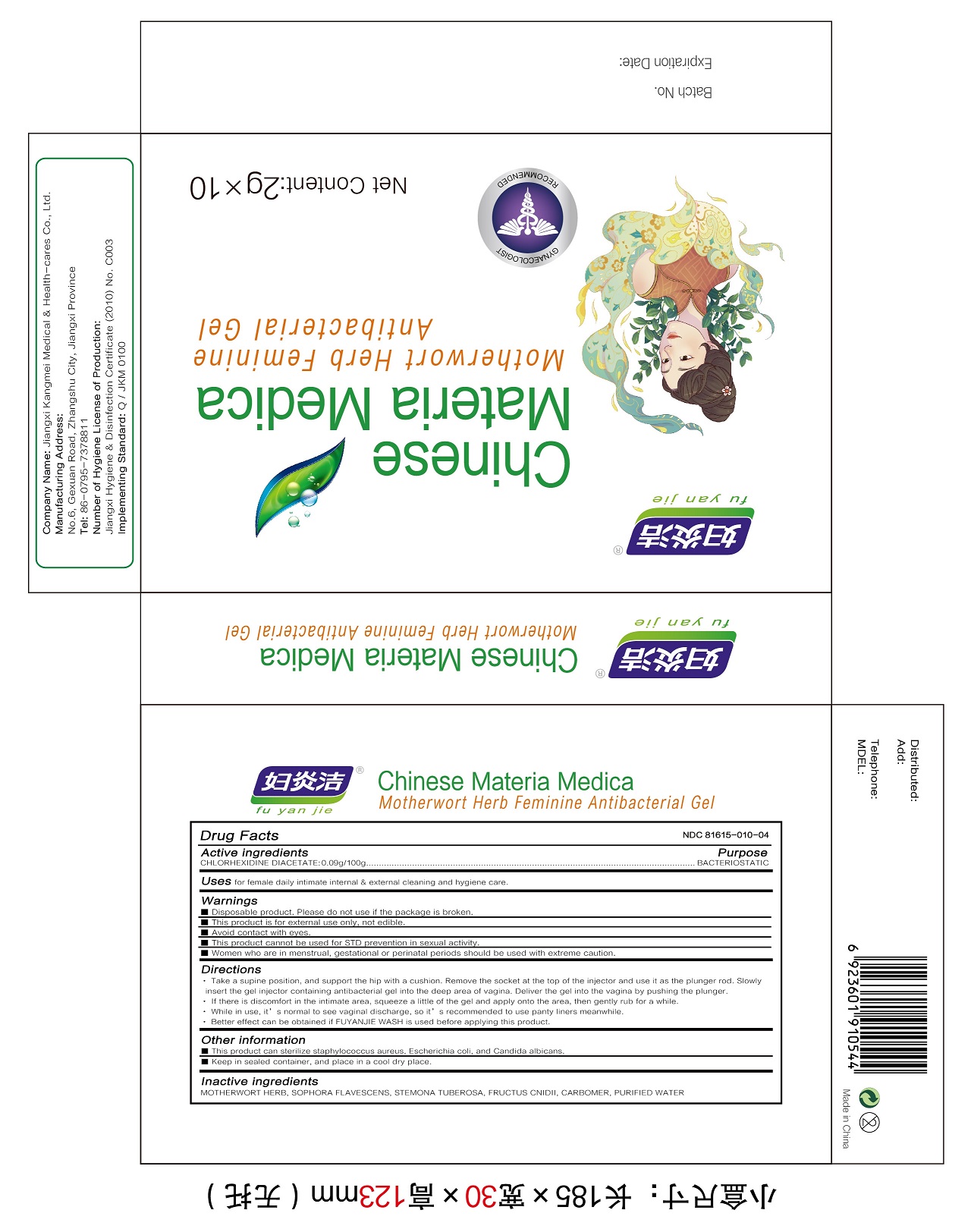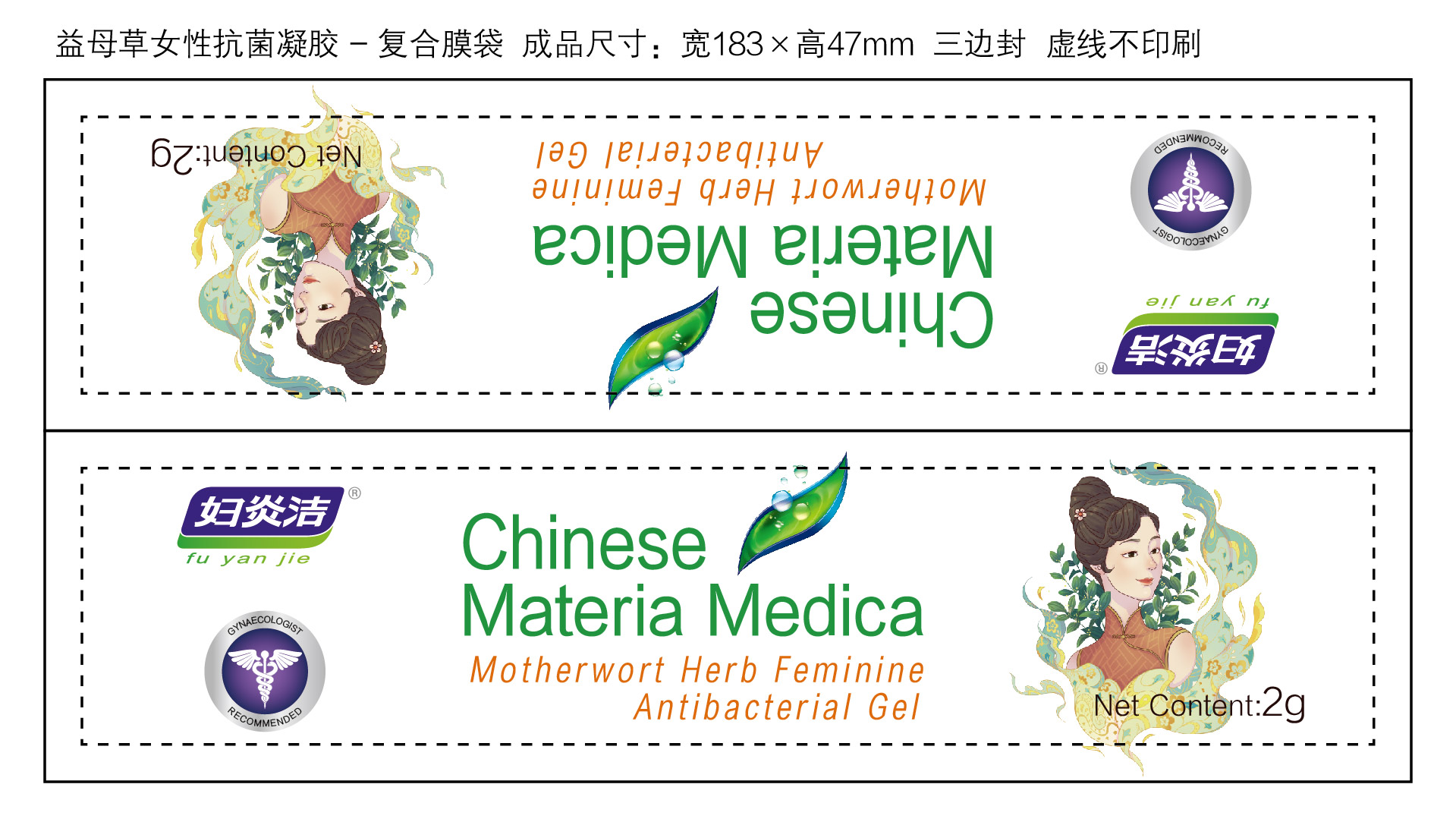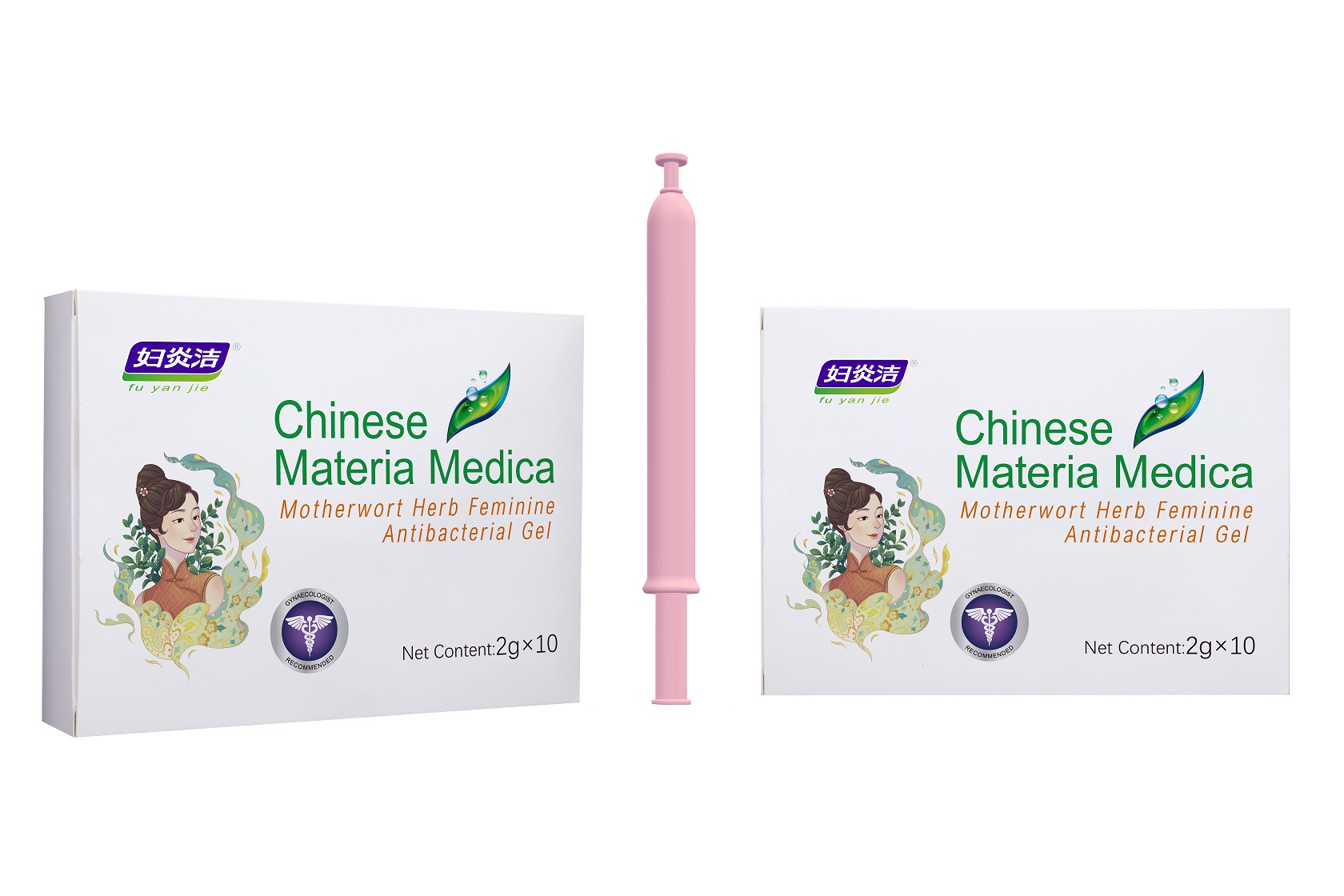 DRUG LABEL: MOTHERWORT HERB FEMININE ANTIBACTERIAL GELS
NDC: 81615-010 | Form: GEL
Manufacturer: Jiangxi Renhetang pharmaceutical chain Co., Ltd.
Category: otc | Type: HUMAN OTC DRUG LABEL
Date: 20210421

ACTIVE INGREDIENTS: CHLORHEXIDINE ACETATE 0.09 g/100 g
INACTIVE INGREDIENTS: OSTHOL; LEONURUS CARDIACA FLOWERING TOP; SOPHORA FLAVESCENS ROOT; WATER; CARBOMER HOMOPOLYMER, UNSPECIFIED TYPE; STEMONA TUBEROSA ROOT

MOTHERWORT HERB FEMININE ANTIBACTERIAL GEL

MOTHERWORT HERB FEMININE ANTIBACTERIAL GEL

Active Ingredient(s)

CHLORHEXIDINE DIACETATE 0.09g/100g

Purpose

BACTERIOSTATIC

Use

Uses for female daily intimate internal & external cleaning and hygiene care.

Warnings

Disposable product. Please do not use if the package is broken.

This product is for external use only, not edible.

Avoid contact with eyes

This product cannot be used for STD prevention in sexual activity.

Women who are in menstrual, gestational or perinatal periods should be used with extreme caution.

When using this product keep out of eyes, ears, and mouth. In case of contact with eyes, rinse eyes thoroughly with water.
Stop use and ask a doctor if irritation or rash occurs. These may be signs of a serious condition.
Keep out of reach of children. If swallowed, get medical help or contact a Poison Control Center right away.

Stop use and ask a doctor if irritation or rash occurs. These may be signs of a serious condition.

Keep out of reach of children. If swallowed, get medical help or contact a Poison Control Center right away.

Directions

1.Take a supine position, and support the hip with a cushion. Remove the socket at the top of the injector and use it as the plunger rod. Slowly insert the gel injector containing antibacterial gel into the deep area of vagina. Deliver the gel into the vagina by pushing the plunger.
2.If there is discomfort in the intimate area, squeeze a little of the gel and apply onto the area, then gently rub for a while.
3.While in use, it’s normal to see vaginal discharge, so it’s recommended to use panty liners meanwhile.
4.Better effect can be obtained if FUYANJIE WASH is used before applying this product.

Other information

This product can sterilize staphylococcus aureus, Escherichia coli, and Candida albicans.

Keep in sealed container, and place in a cool dry place.

Inactive ingredients

MOTHERWORT HERB
SOPHORA FLAVESCENS
STEMONA TUBEROSA
FRUCTUS CNIDII
CARBOMER
PURIFIED WATER